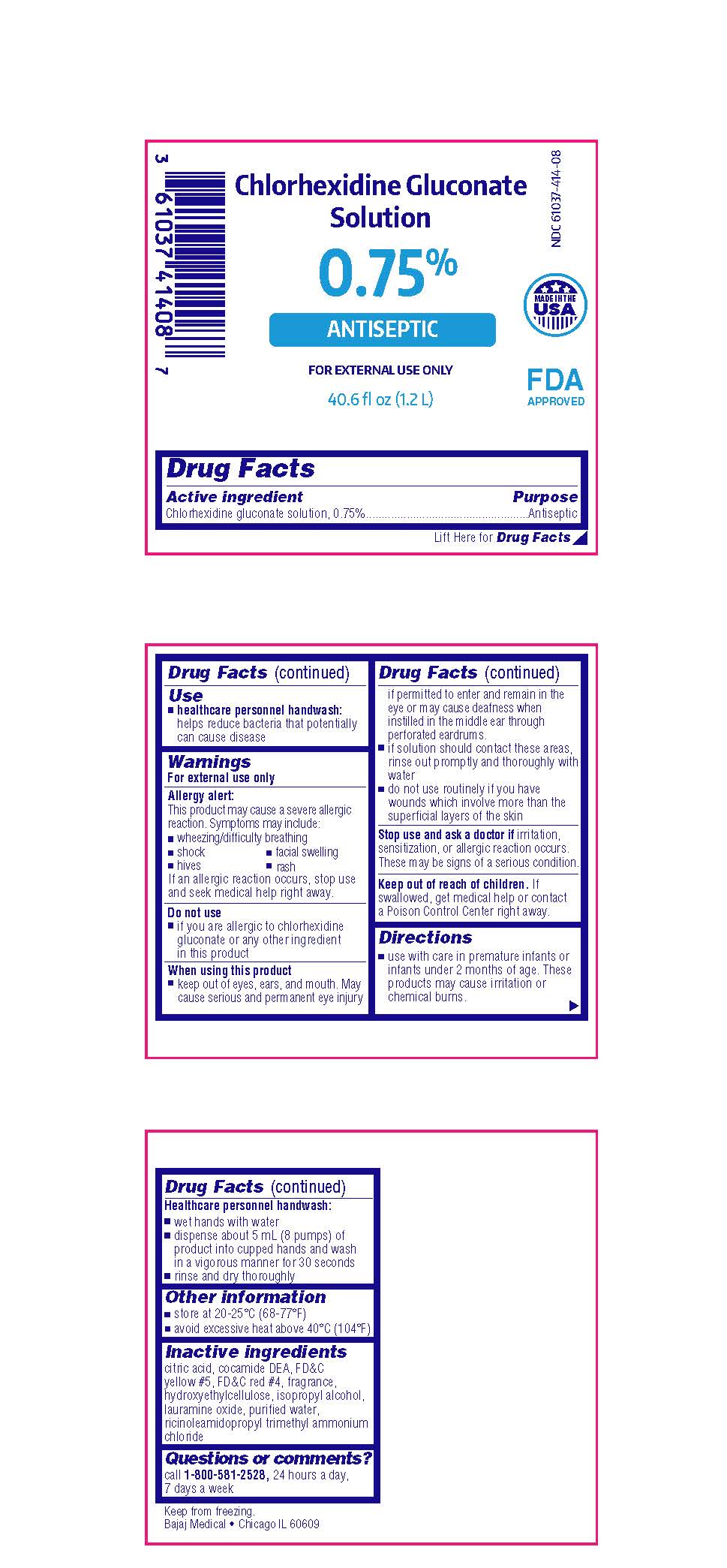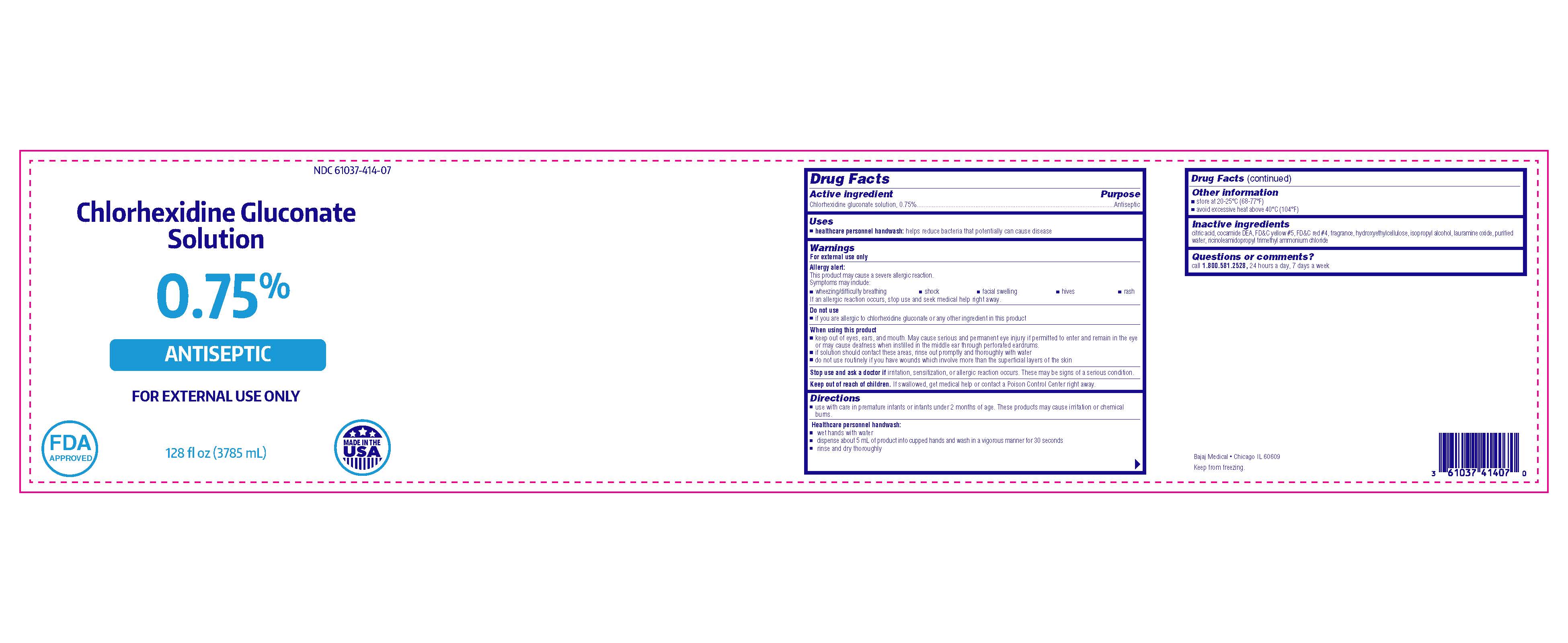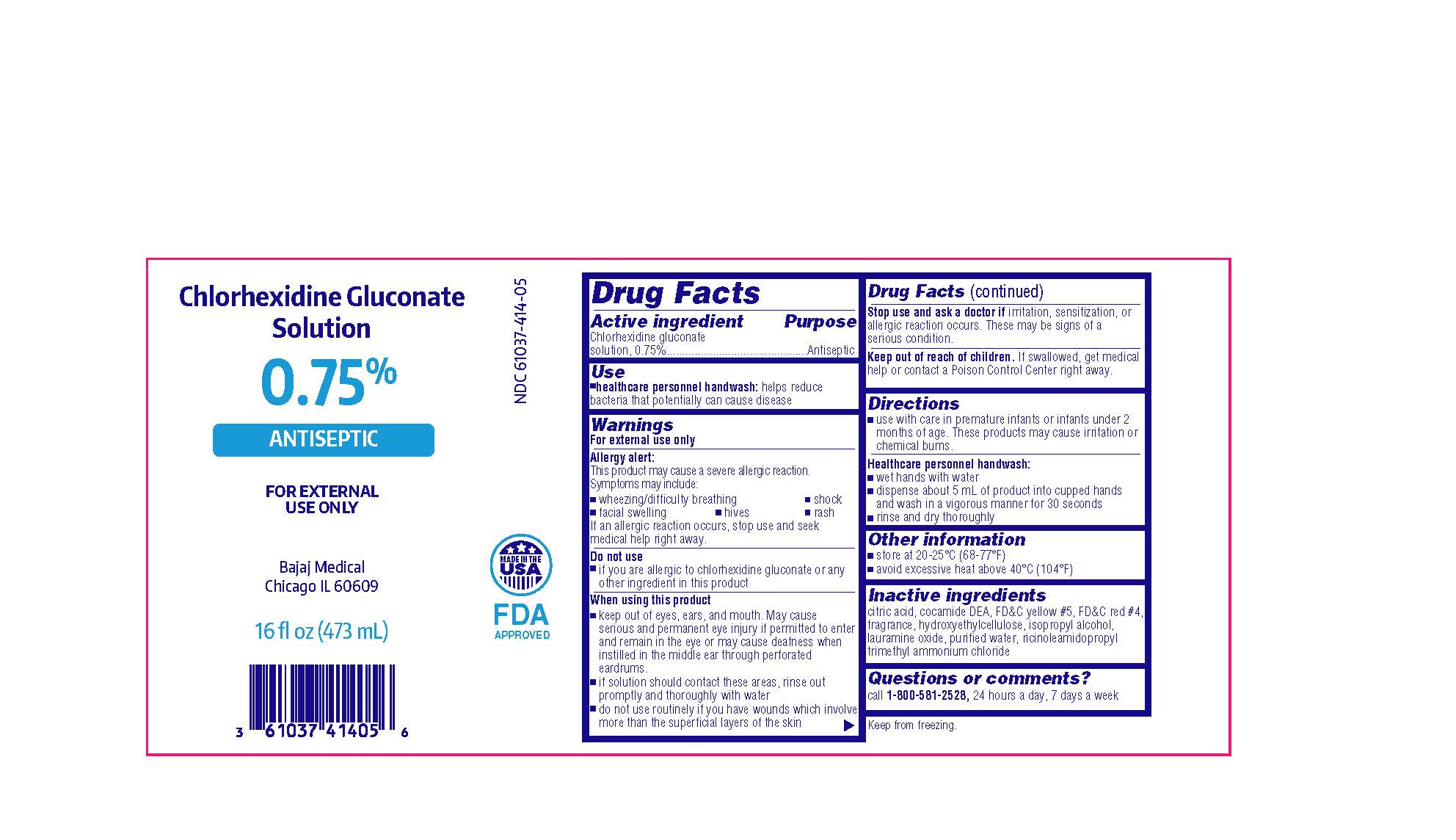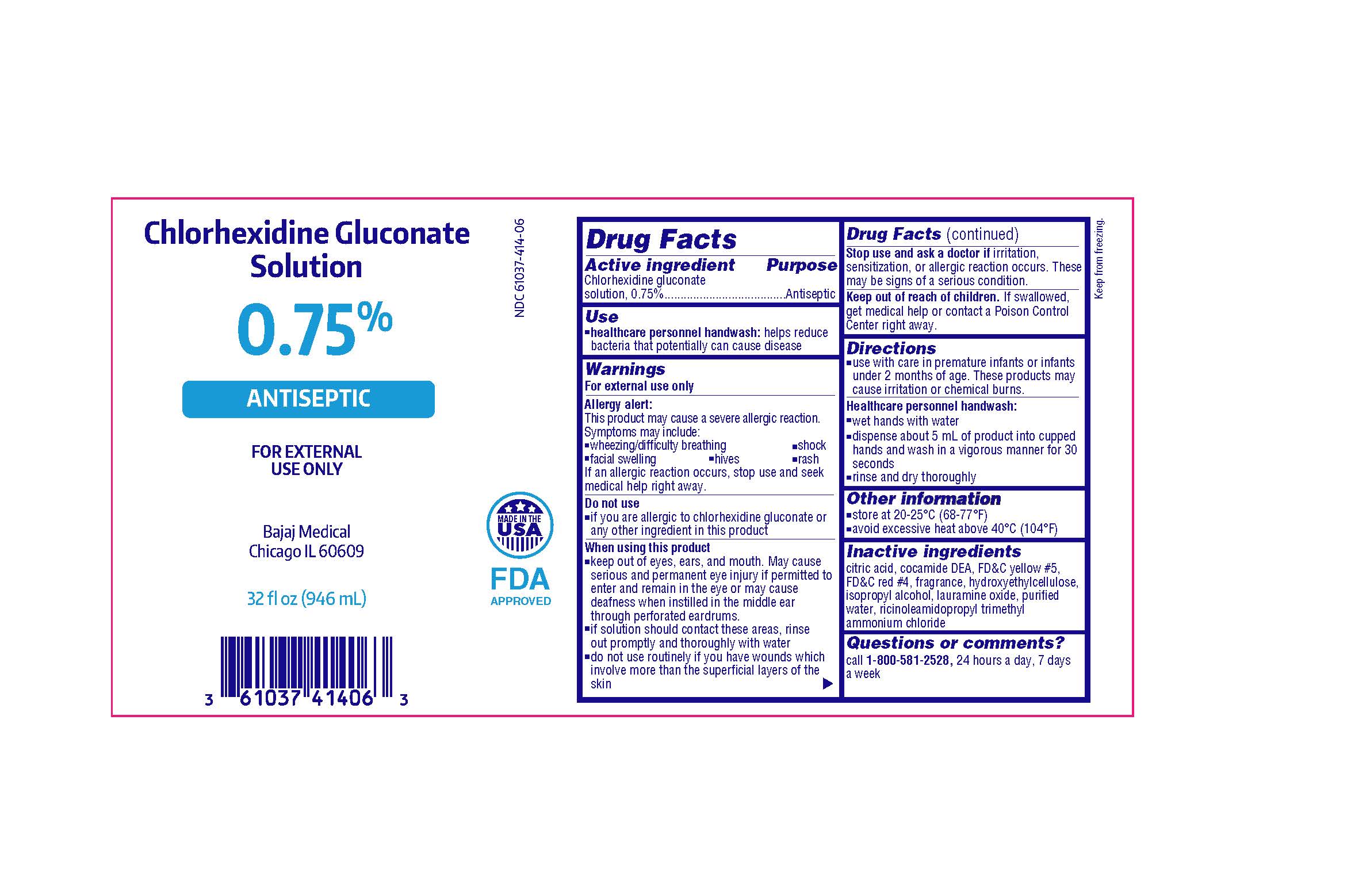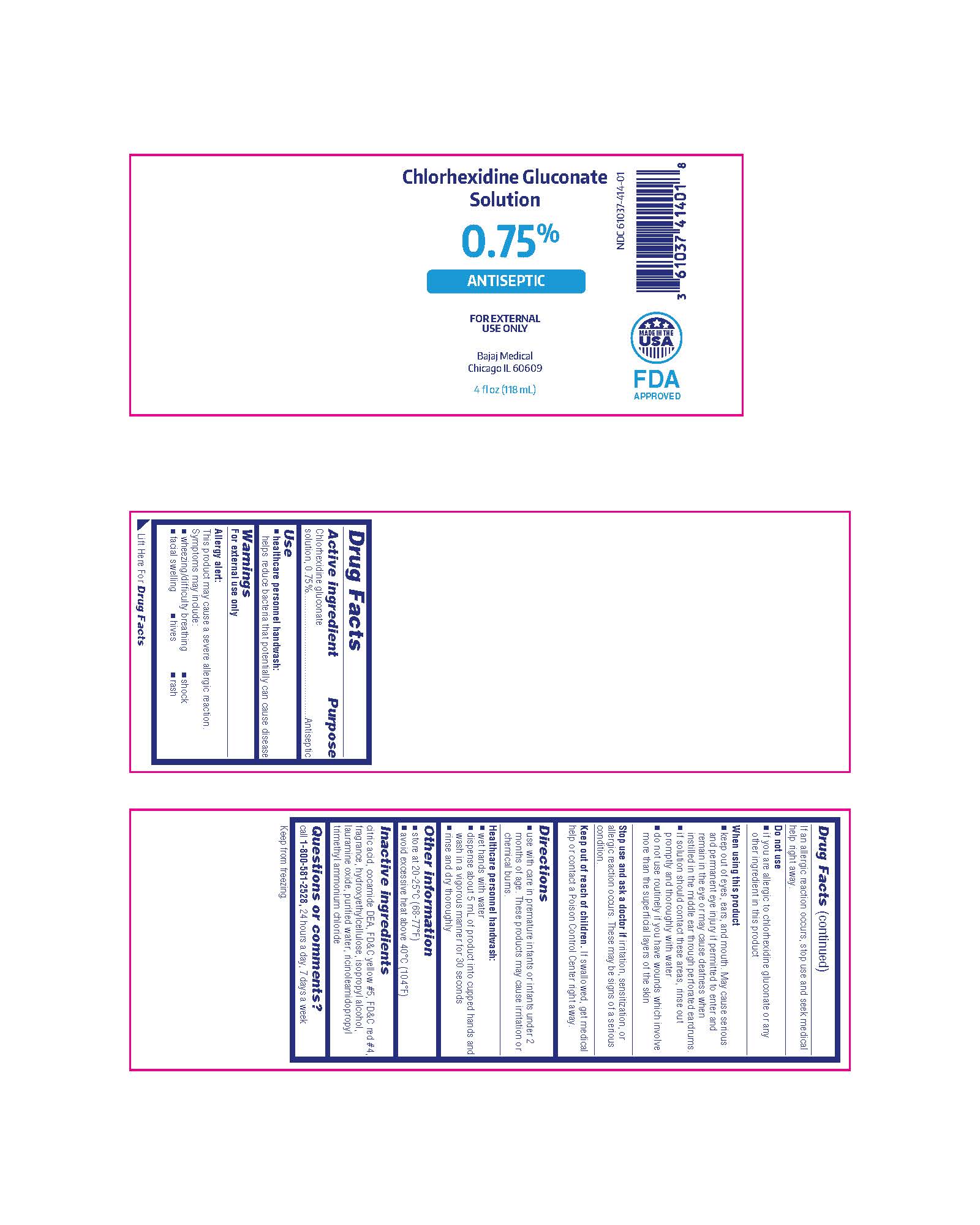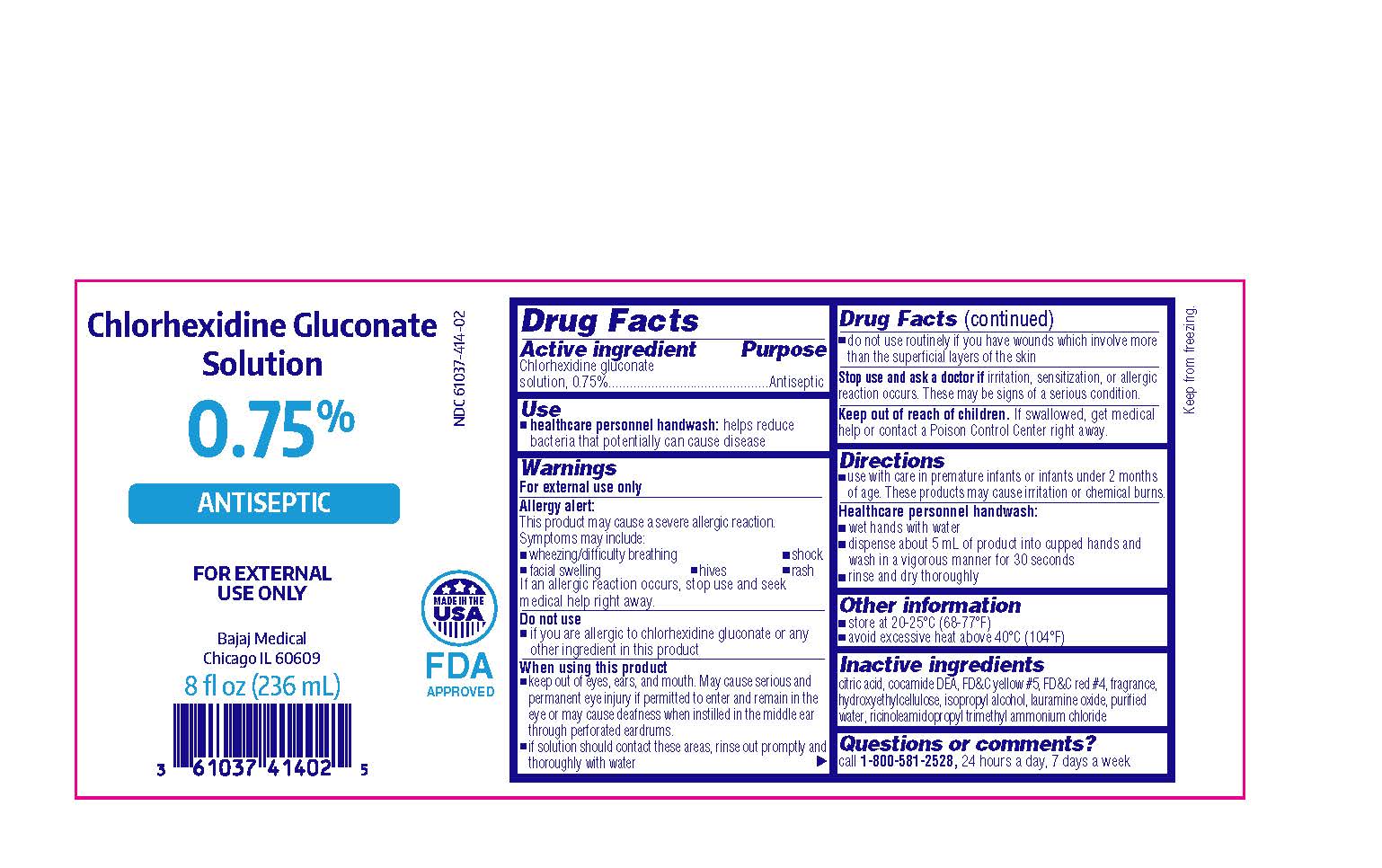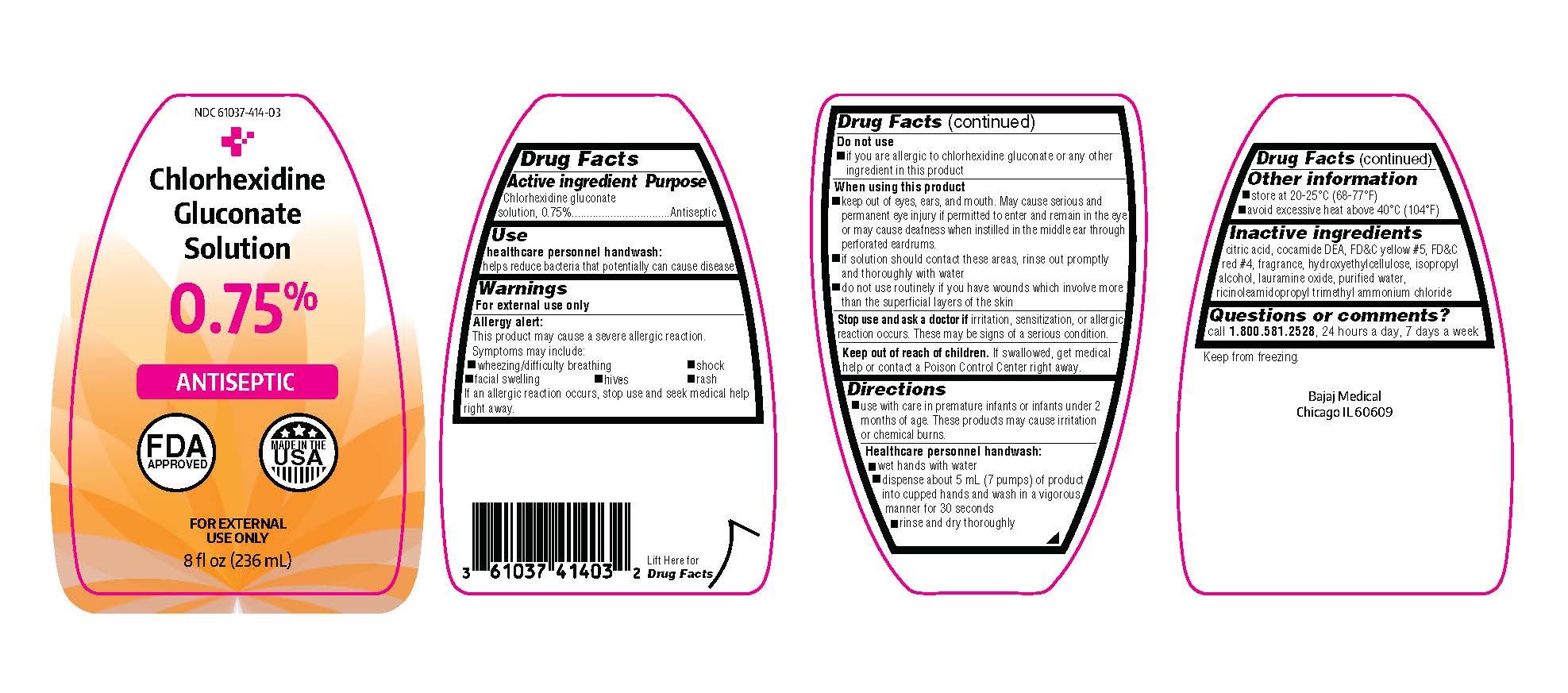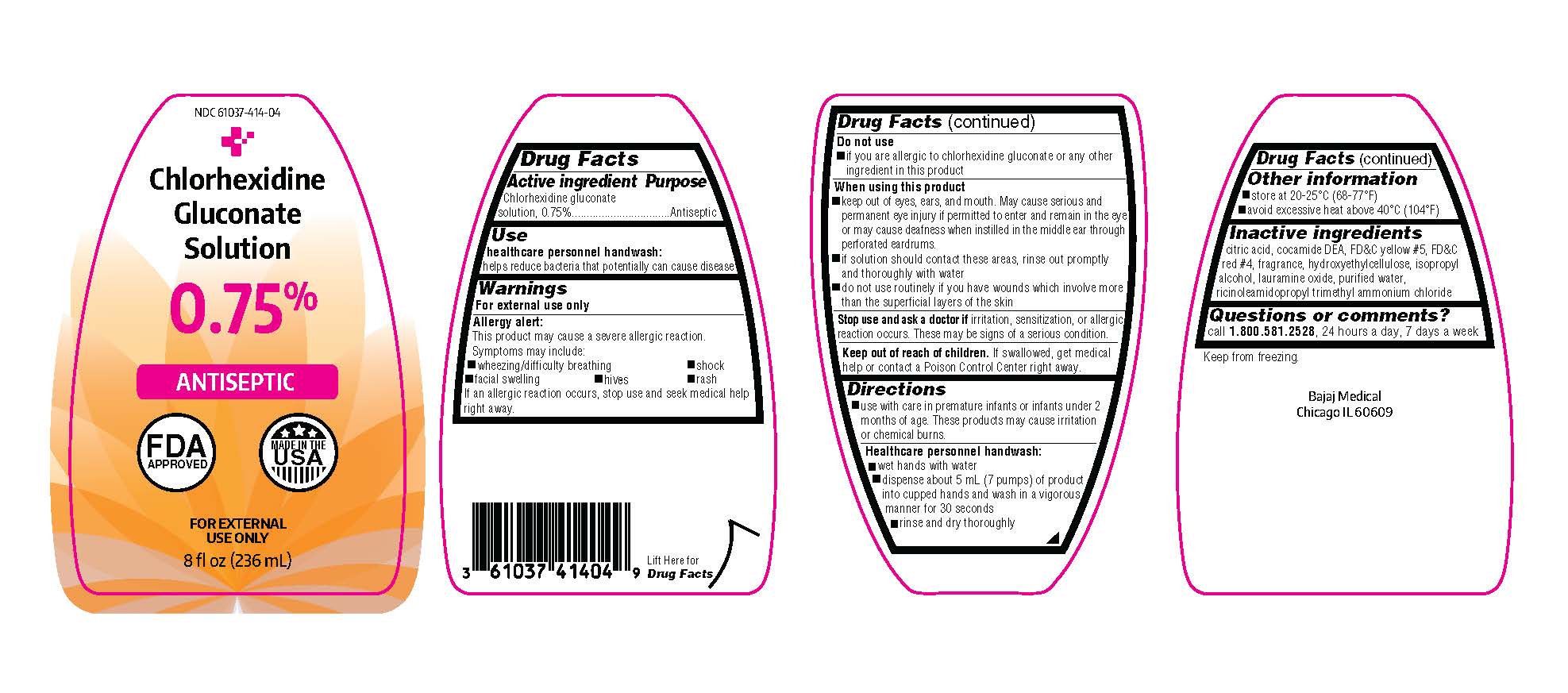 DRUG LABEL: Chlorhexidine Gluconate Solution 0.75% Antiseptic
NDC: 61037-414 | Form: SOLUTION
Manufacturer: Bajaj Medical, LLC
Category: otc | Type: HUMAN OTC DRUG LABEL
Date: 20221226

ACTIVE INGREDIENTS: CHLORHEXIDINE GLUCONATE 0.75 mg/100 mL
INACTIVE INGREDIENTS: COCO DIETHANOLAMIDE; HYDROXYETHYL CELLULOSE (140 CPS AT 5%); ISOPROPYL ALCOHOL; LAURAMINE OXIDE; RICINOLEAMIDOPROPYLTRIMONIUM CHLORIDE; WATER; CITRIC ACID MONOHYDRATE; FD&C YELLOW NO. 5; FD&C RED NO. 4

Drug Facts

Active ingredient

Chlorhexidine gluconate solution, 0.75%

Purpose

Antiseptic

Use

- healthcare personnel handwash: helps reduce bacteria that potentially can cause disease

Warnings

For external use only

Allergy alert:

This product may cause a severe allergic reaction.

Symptoms may include:

- wheezing/difficulty breathing
- shock
- facial swelling
- hives
- rash

If an allergic reaction occurs, stop use and seek medical help right away.

Do not use

- if you are allergic to chlorhexidine gluconate or any other ingredient in this product

When using this product

- keep out of eyes, ears, and mouth. May cause serious and permanent eye injury if permitted to enter and remain in the eye or may cause deafness when instilled in the middle ear through perforated eardrums.
- if solution should contact these areas, rinse out promptly and thoroughly with water
- do not use routinely if you have wounds which involve more than the superficial layers of the skin

Stop use and ask a doctor if

irritation, sensitization, or allergic reaction occurs. These may be signs of a serious condition.

Keep out of reach of children.

If swallowed, get medical help or contact a Poison Control Center right away.

Directions

- use with care in premature infants and infants under 2 months of age. These products may cause irritation or chemical burns.

Healthcare personnel handwash:

- wet hands with water
- dispense about 5 mL of product into cupped hands and wash in a vigorous manner for 30 seconds
- rinse and dry thoroughly

Other information

- store at 20-25°C (68-77°F)
- avoid excessive heat above 40°C (104°F)

Inactive ingredients

citric acid, cocamide DEA, FD&C yellow #5, FD&C red #4, fragrance, hydroxyethylcellulose, isopropyl alcohol, lauramine oxide, purified water, ricinoleamidopropyl trimethyl ammonium chloride

Questions or comments?

call 1-800-581-2528, 24 hours a day, 7 days a week

Package/Label Principal Display Panel

Chlorhexidine Gluconate Solution

0.75%

ANTISEPTIC

FOR EXTERNAL USE ONLY

Bajaj Medical

Chicago IL 60609

4 fl oz (118 mL)

NDC 61037-414-01

MADE IN THE USA

FDA APPROVED

Chlorhexidine Gluconate Solution

0.75%

ANTISEPTIC

FOR EXTERNAL USE ONLY

Bajaj Medical

Chicago IL 60609

8 fl oz (236 mL)

NDC 61037-414-02

MADE IN THE USA

FDA APPROVED

Chlorhexidine Gluconate Solution

0.75%

ANTISEPTIC

FOR EXTERNAL USE ONLY

Bajaj Medical

Chicago IL 60609

16 fl oz (473 mL)

NDC 61037-414-05

MADE IN THE USA

FDA APPROVED

Chlorhexidine Gluconate Solution

0.75%

ANTISEPTIC

FOR EXTERNAL USE ONLY

Bajaj Medical

Chicago IL 60609

32 fl oz (946 mL)

NDC 61037-414-06

MADE IN THE USA

FDA APPROVED

Chlorhexidine Gluconate Solution

0.75%

ANTISEPTIC

FOR EXTERNAL USE ONLY

Bajaj Medical

Chicago IL 60609

128 fl oz (3785 mL)

NDC 61037-414-07

MADE IN THE USA

FDA APPROVED

Chlorhexidine Gluconate Solution

0.75%

ANTISEPTIC

FOR EXTERNAL USE ONLY

Bajaj Medical

Chicago IL 60609

8 fl oz (236 mL)

NDC 61037-414-03

MADE IN THE USA

FDA APPROVED

Chlorhexidine Gluconate Solution

0.75%

ANTISEPTIC

FOR EXTERNAL USE ONLY

Bajaj Medical

Chicago IL 60609

8 fl oz (236 mL)

NDC 61037-414-04

MADE IN THE USA

FDA APPROVED

Chlorhexidine Gluconate Solution

0.75%

ANTISEPTIC

FOR EXTERNAL USE ONLY

Bajaj Medical

Chicago IL 60609

40.6 fl oz (1.2 L)

NDC 61037-414-08

MADE IN THE USA

FDA APPROVED

STORAGE AND HANDLING

Keep from freezing.